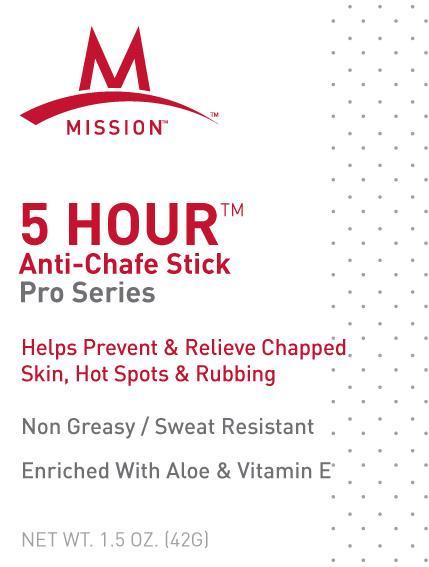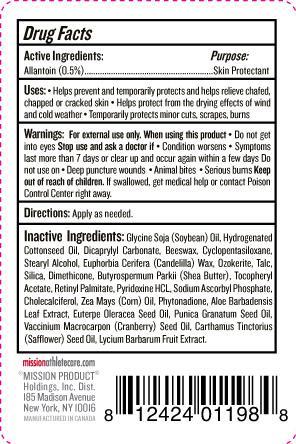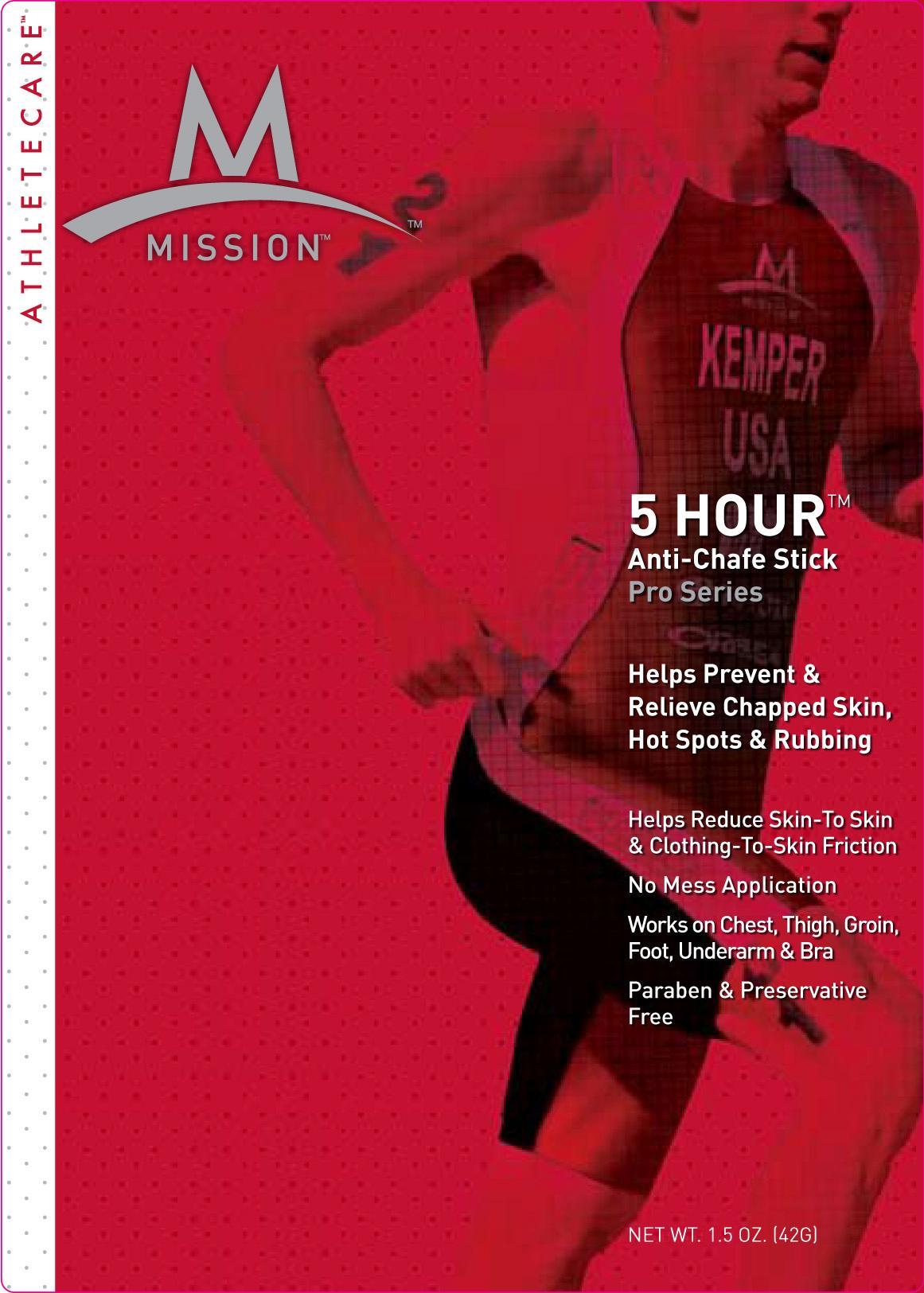 DRUG LABEL: Anti-Chafe Stick
NDC: 76347-125 | Form: STICK
Manufacturer: Mission Product Holdings
Category: otc | Type: HUMAN OTC DRUG LABEL
Date: 20130212

ACTIVE INGREDIENTS: ALLANTOIN 0.5 g/100 g
INACTIVE INGREDIENTS: HYDROGENATED COTTONSEED OIL; DICAPRYLYL CARBONATE; CYCLOMETHICONE 5; STEARYL ALCOHOL; CANDELILLA WAX; CERESIN; TALC; SILICON DIOXIDE; DIMETHICONE; SHEA BUTTER; VITAMIN A PALMITATE; PYRIDOXINE HYDROCHLORIDE; SODIUM ASCORBYL PHOSPHATE; CHOLECALCIFEROL; ALOE VERA LEAF; POMEGRANATE SEED OIL ; CRANBERRY SEED OIL; SAFFLOWER OIL; LYCIUM BARBARUM FRUIT

Anti-chafe Stick Pro Series

Active ingredients Purpose

Allantoin (0.5%) Skin protectant

PURPOSE

Uses: Helps Prevent and temporarily relieve chafed, chapped or cracked skin

Helps protect from the drying effects of wind and cold weather

Temporarily protects minor cuts, scrapes , burns

Keep out of reach of children

Stop use and ask a doctor if

Conditions worsens

symptoms last more than 7 days or clear up and occur again within a few days

Warnings: For external use only

When using this product: do not get into eyes

Do not use on: deep puncture wounds, Animal bites , Serious burns

If swallowed,get medical or contact Poison Control Center

DOSAGE AND ADMINISTRATION

Directions: apply as needed

INACTIVE INGREDIENT

Inactive ingredients: Glycine soja (soybean) oil, hydrogenated cottonseed oil, dicaprylyl carbonate, beeswax, cyclopentasiloxane, stearyl alcohol, Euphorbia Cerifera (candelilla) wax, ozokerite, talc, silica, dimethicone, butyrospermum parkii (shea butter), tocopheryl acetate, retinyl palmitate, pyridoxine HCL, Sodium ascorbyl phosphate, cholecalciferol, zea mays (corn) oil, phytonidone, aloe barbadensis leaf extract, euterpe oleracea seed oil, punica granatum seed oil, vaccinium macrocarpon (cranberry) seed oil, carthamus tinctorius (safflower) seed oil, lycium barbarum fruit extract.

PACKAGE LABEL

5 hour (TM)

Anti-chafe stick

Pro series

Net. Wt. 1.5 oz (42 G)